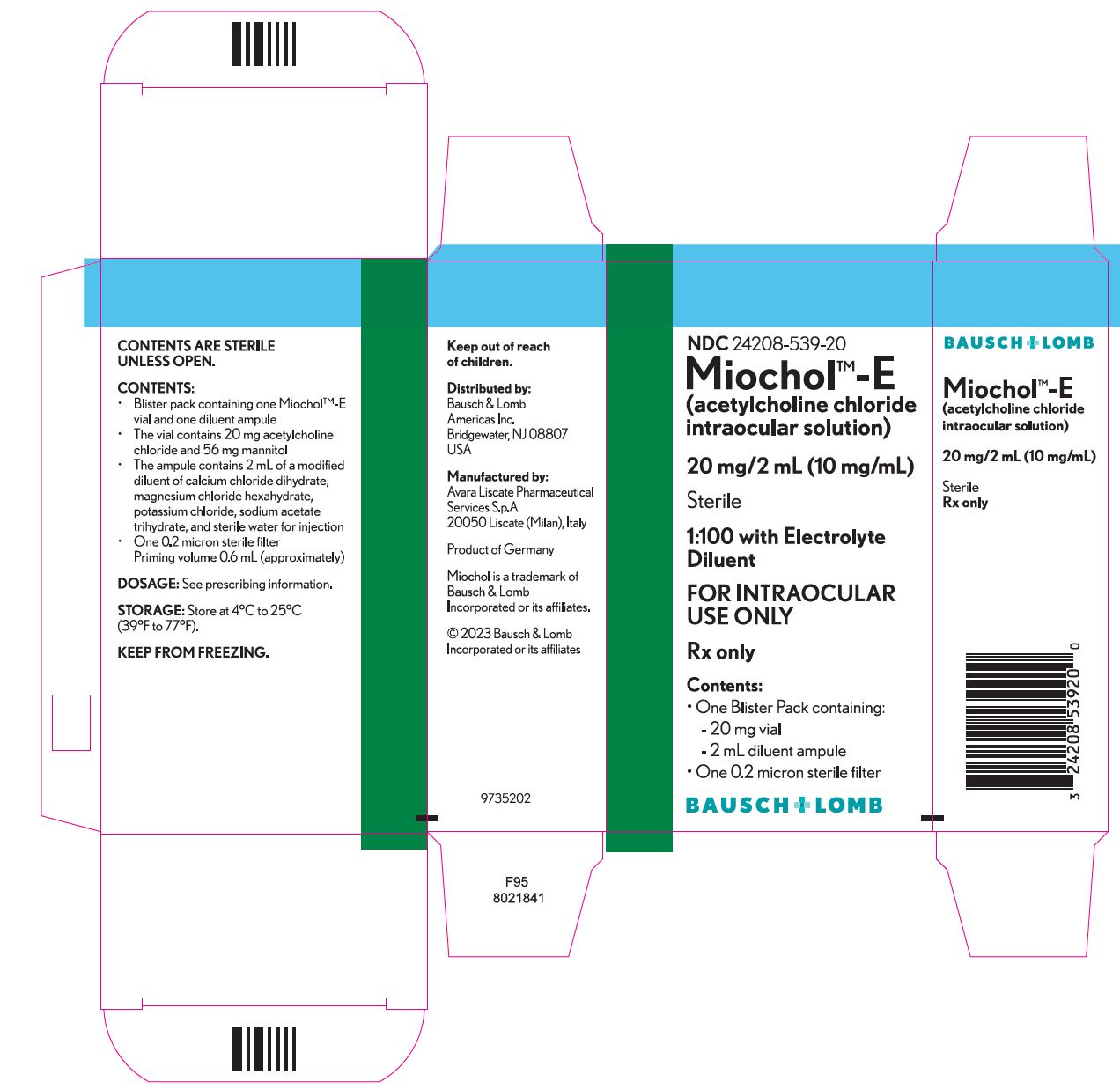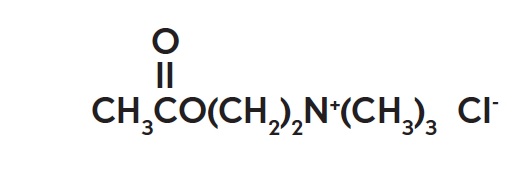 DRUG LABEL: Miochol E
NDC: 24208-539 | Form: KIT | Route: INTRAOCULAR
Manufacturer: Bausch & Lomb Incorporated
Category: prescription | Type: HUMAN PRESCRIPTION DRUG LABEL
Date: 20230317

ACTIVE INGREDIENTS: ACETYLCHOLINE CHLORIDE 20 mg/2 mL
INACTIVE INGREDIENTS: MANNITOL 56 mg/2 mL; CALCIUM CHLORIDE; MAGNESIUM CHLORIDE; POTASSIUM CHLORIDE; SODIUM ACETATE; WATER

Miochol™-E
(acetylcholine chloride
intraocular solution)
20 mg/2 mL (10 mg/mL)
Sterile
1:100 with Electrolyte Diluent
FOR INTRAOCULAR USE ONLY

DESCRIPTION

Miochol™-E (acetylcholine chloride intraocular solution) is a parasympathomimetic preparation for intraocular use. It is packaged in a blister pack containing one vial and one diluent ampule. The vial contains 20 mg acetylcholine chloride and 56 mg mannitol. The accompanying ampule contains 2 mL of a modified diluent of calcium chloride dihydrate, magnesium chloride hexahydrate, potassium chloride, sodium acetate trihydrate, and sterile water for injection.

The reconstituted liquid will be a sterile isotonic solution (275–330 milliosmoles/kg) containing 20 mg acetylcholine chloride (1:100 solution) and 2.8% mannitol. The pH range is 5.0–8.2. Mannitol is used in the process of lyophilizing acetylcholine chloride, and is not considered an active ingredient.

The chemical name for acetylcholine chloride, C7H16ClNO2, is Ethanaminium, 2-(acetyloxy)-N,N,N-trimethyl-, chloride and is represented by the following chemical structure:

CLINICAL PHARMACOLOGY

Acetylcholine is a naturally occurring neurohormone which mediates nerve impulse transmission at all cholinergic sites involving somatic and autonomic nerves. After release from the nerve ending, acetylcholine is rapidly inactivated by the enzyme acetylcholinesterase by hydrolysis to acetic acid and choline.

Direct application of acetylcholine to the iris will cause rapid miosis of short duration. Topical ocular instillation of acetylcholine to the intact eye causes no discernible response as cholinesterase destroys the molecule more rapidly than it can penetrate the cornea.

INDICATIONS AND USAGE

To obtain miosis of the iris in seconds after delivery of the lens in cataract surgery, in penetrating keratoplasty, iridectomy, and other anterior segment surgery where rapid miosis may be required.

CONTRAINDICATIONS

Miochol-E is contraindicated in persons with a known hypersensitivity to any component of this product.

WARNINGS

DO NOT GAS STERILIZE. If blister or peelable backing is damaged or broken, sterility of the enclosed vial and ampule cannot be assured. Open under aseptic conditions only.

PRECAUTIONS

General

If miosis is to be obtained quickly with Miochol-E, anatomical hindrances to miosis, such as anterior or posterior synechiae, must be released, prior to administration of Miochol-E. During cataract surgery, use Miochol-E only after delivery of the lens.

Aqueous solutions of acetylcholine chloride are unstable. Prepare solution immediately before use. Do not use solution which is not clear and colorless. Discard any solution that has not been used.

Drug Interactions

Although clinical studies with acetylcholine chloride and animal studies with acetylcholine or carbachol revealed no interference, and there is no known pharmacological basis for an interaction, there have been reports that acetylcholine chloride and carbachol have been ineffective when used in patients treated with topical nonsteroidal anti-inflammatory agents.

Pediatric Use

Safety and effectiveness in pediatric patients have not been established.

ADVERSE REACTIONS

Infrequent cases of corneal edema, corneal clouding, and corneal decompensation have been reported with the use of intraocular acetylcholine.

Adverse reactions have been reported rarely, which are indicative of systemic absorption. These include bradycardia, hypotension, flushing, breathing difficulties, and sweating.

To report SUSPECTED ADVERSE REACTIONS, contact Bausch & Lomb Incorporated at 1-800-553-5340 or FDA at 1-800-FDA-1088 or www.fda.gov/medwatch.

OVERDOSAGE

Atropine sulfate (0.5 to 1 mg) should be given intramuscularly or intravenously and should be readily available to counteract possible overdosage. Epinephrine (0.1 to 1 mg subcutaneously) is also of value in overcoming severe cardiovascular or bronchoconstrictor responses.

DOSAGE AND ADMINISTRATION

Miochol™-E (acetylcholine chloride intraocular solution) is instilled into the anterior chamber before or after securing one or more sutures.

Instillation should be gentle and parallel to the iris face and tangential to pupil border.

If there are no mechanical hindrances, the pupil starts to constrict in seconds and the peripheral iris is drawn away from the angle of the anterior chamber. Any anatomical hindrance to miosis must be released to permit the desired effect of the drug. In most cases, 0.5 to 2 mL produces satisfactory miosis. Note that the syringe filter supplied with Miochol-E has a priming volume of 0.6 mL (approximately).

In cataract surgery, use Miochol-E only after delivery of the lens.

Aqueous solutions of acetylcholine chloride are unstable. Prepare solution immediately before use. Do not use solution that is not clear and colorless. Discard any solution that has not been used.

DIRECTIONS FOR PREPARING MIOCHOL™-E:

STERILE UNLESS PACKAGE OPEN OR BROKEN

1. Inspect the unopened blister, vial, and ampule to ensure that they are all intact. Peel open the blister under a sterile field. Maintain sterility of the outer containers of the vial and ampule during preparation of solution.
2. Aseptically attach a sterile 18–20 gauge, beveled needle to the luer tip of a sterile disposable syringe with a twisting motion to assure a secure fit.
3. Break open the ampule containing the diluent. The One Point Cut (OPC) ampule must be opened as follows: Hold the bottom part of the ampule with the thumb pointing to the colored dot. Grasp the top of the ampule with the other hand, positioning the thumb at the colored dot, and press back to break at the existing cut under the dot.
4. Remove the needle protector and withdraw the diluent from the ampule into the syringe. Discard the ampule.
5. Remove and discard the cap from the top of the vial.
6. Insert the needle through the center of the vial stopper, and transfer the diluent from the syringe to the vial. Shake gently to dissolve the powder.
7. Slowly withdraw the solution from the vial through the needle into the syringe. Discard the needle.
8. Aseptically open the syringe filter pouch, and attach the filter onto the luer tip of the syringe with a twisting motion to assure a secure fit.
9. Aseptically attach a sterile blunt tip irrigation cannula to the male luer of the filter prior to intraocular irrigation.

Discard the filter appropriately after use.

Do not reuse the syringe filter.

Do not aspirate and inject through the same filter.

HOW SUPPLIED

Miochol™-E

(acetylcholine chloride intraocular solution)............................NDC 24208-539-20

One blister pack containing the following components:

- Vial of 20 mg acetylcholine chloride powder for intraocular solution
- Ampule of 2 mL diluent

One 0.2 micron sterile filter

- Priming volume 0.6 mL (approximately)

Storage

Store at 4°C to 25°C (39°F to 77°F).

KEEP FROM FREEZING.

Keep out of reach of children.

Distributed by:

Bausch & Lomb Americas Inc.

Bridgewater, NJ 08807 USA

Manufactured by:

Avara Liscate Pharmaceutical Services S.p.A

20050 Liscate (Milan), Italy

Miochol is a trademark of Bausch & Lomb Incorporated or its affiliates.

© 2023 Bausch & Lomb Incorporated or its affiliates

Rev. 03/2023 | 9735301

PACKAGE/LABEL PRINCIPAL DISPLAY PANEL

NDC 24208-539-20

Miochol TM -E

(acetylcholine chloride intraocular solution)

20 mg/2 mL (10 mg/mL)

Sterile

1:100 with Electrolyte

Diluent

FOR INTRAOCULAR

USE ONLY

Rx only

Contents:

- One Blister Pack containing:
-20 mg vial
-2 mL diluent ampule
- One 0.2 micron sterile filter

BAUSCH + LOMB

9735202